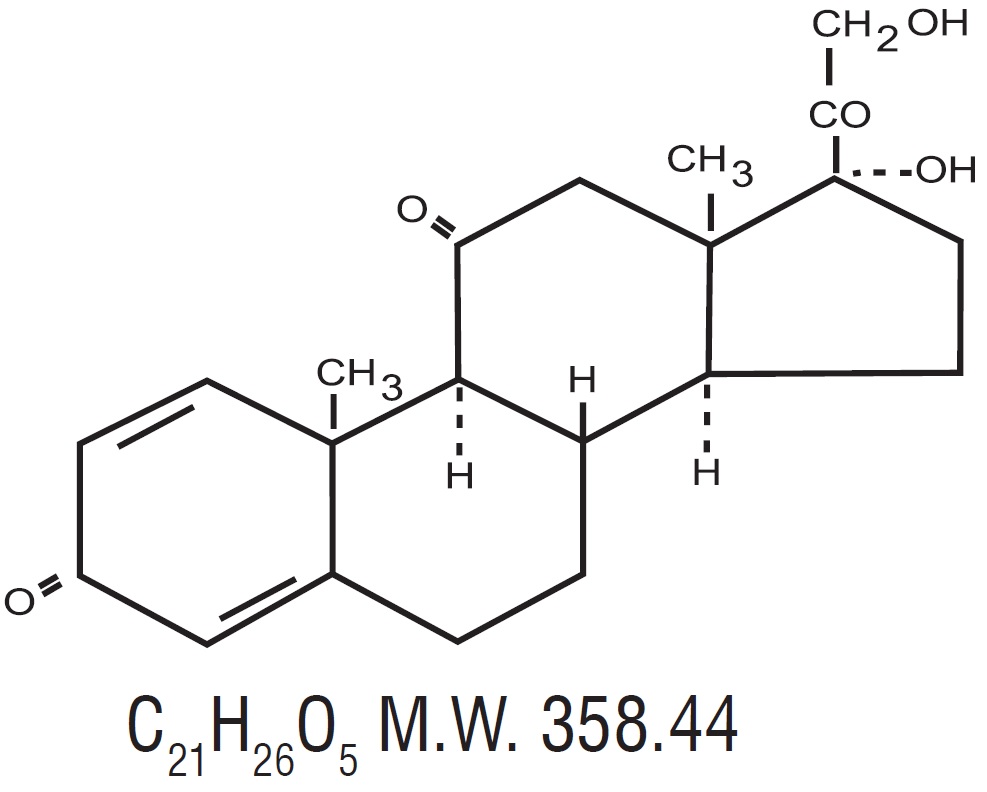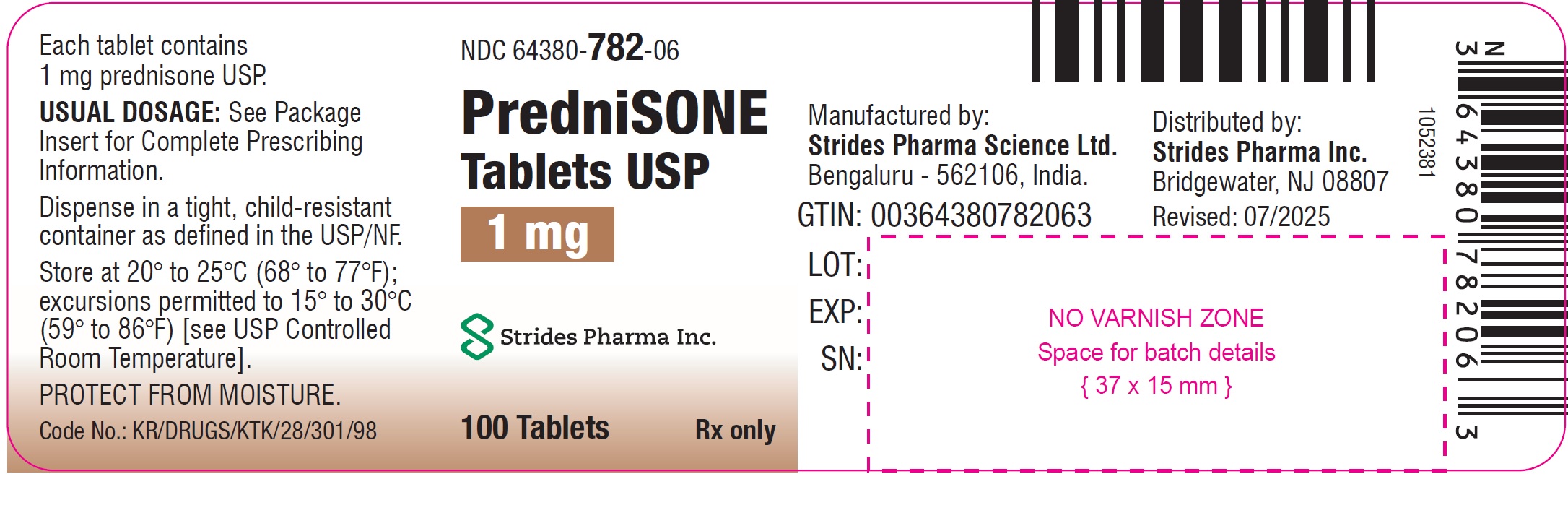 DRUG LABEL: prednisone
NDC: 64380-782 | Form: TABLET
Manufacturer: Strides Pharma Science Limited
Category: prescription | Type: HUMAN PRESCRIPTION DRUG LABEL
Date: 20251203

ACTIVE INGREDIENTS: PREDNISONE 1 mg/1 1
INACTIVE INGREDIENTS: LACTOSE MONOHYDRATE; MAGNESIUM STEARATE; CELLULOSE, MICROCRYSTALLINE; STARCH, CORN; SODIUM STARCH GLYCOLATE TYPE A POTATO

PredniSONE Tablets USP
Rx only

DESCRIPTION

Prednisone Tablets USP are available for oral administration containing 1 mg of prednisone USP. Each tablet contains the following inactive ingredients: lactose monohydrate, magnesium stearate, microcrystalline cellulose, pregelatinized starch (maize starch), sodium starch glycolate.

Prednisone tablets USP contain prednisone which is a glucocorticoid. Glucocorticoids are adrenocortical steroids, both naturally occurring and synthetic, which are readily absorbed from the gastrointestinal tract. The chemical name for prednisone is 17, 21-dihydroxypregna-1,4-diene-3,11,20-trione. The structural formula is represented below:

Prednisone is a white to partially white, crystalline powder. It is very slightly soluble in water; slightly soluble in alcohol, chloroform, dioxane, and methanol.

FDA approved dissolution test specifications differ from USP.

CLINICAL PHARMACOLOGY

Naturally occurring glucocorticoids (hydrocortisone and cortisone), which also have salt-retaining properties, are used as replacement therapy in adrenocortical deficiency states. Their synthetic analogs are primarily used for their potent anti-inflammatory effects in disorders of many organ systems.

Glucocorticoids cause profound and varied metabolic effects. In addition, they modify the body's immune responses to diverse stimuli.

INDICATIONS AND USAGE

Prednisone tablets USP are indicated in the following conditions:

Endocrine disorders: primary or secondary adrenocortical insufficiency (hydrocortisone or cortisone is the first choice; synthetic analogs may be used in conjunction with mineralocorticoids where applicable; in infancy mineralocorticoid supplementation is of particular importance), congenital adrenal hyperplasia, nonsuppurative thyroiditis, hypercalcemia associated with cancer.

Rheumatic disorders: as adjunctive therapy for short-term administration (to tide the patient over an acute episode or exacerbation) in: psoriatic arthritis; rheumatoid arthritis, including juvenile rheumatoid arthritis (selected cases may require low-dose maintenance therapy); ankylosing spondylitis; acute and subacute bursitis; acute nonspecific tenosynovitis; acute gouty arthritis; posttraumatic osteoarthritis; synovitis of osteoarthritis; epicondylitis.

Collagen Diseases: during an exacerbation or as maintenance therapy in selected cases of: systemic lupus erythematosus, acute rheumatic carditis.

Dermatologic Diseases: pemphigus, bullous dermatitis herpetiformis, severe erythema multiforme (Stevens-Johnson syndrome), exfoliative dermatitis, mycosis fungoides, severe psoriasis, severe seborrheic dermatitis.

Allergic States: control of severe or incapacitating allergic conditions intractable to adequate trials of conventional treatment: seasonal or perennial allergic rhinitis, serum sickness, bronchial asthma, contact dermatitis, atopic dermatitis, drug hypersensitivity reactions.

Ophthalmic Diseases: severe acute and chronic allergic and inflammatory processes involving the eye and its adnexa, such as: allergic conjunctivitis, keratitis, allergic corneal marginal ulcers, herpes zoster ophthalmicus, iritis and iridocyclitis, chorioretinitis, anterior segment inflammation, diffuse posterior uveitis and choroiditis, optic neuritis, sympathetic ophthalmia.

Respiratory Diseases: symptomatic sarcoidosis, Loeffler's syndrome not manageable by other means, berylliosis, fulminating or disseminated pulmonary tuberculosis when used concurrently with appropriate antituberculous chemotherapy, aspiration pneumonitis.

Hematologic Disorders: idiopathic thrombocytopenic purpura in adults, secondary thrombocytopenia in adults, acquired (autoimmune) hemolytic anemia, erythroblastopenia (RBC anemia), congenital (erythroid) hypoplastic anemia.

Neoplastic Diseases: for palliative management of: leukemias and lymphomas in adults, acute leukemia of childhood.

Edematous States: to induce a diuresis or remission of proteinuria in the nephrotic syndrome, without uremia, of the idiopathic type or that due to lupus erythematosus.

Gastrointestinal Diseases: to tide the patient over a critical period of the disease in: ulcerative colitis, regional enteritis.

Miscellaneous: tuberculous meningitis with subarachnoid block or impending block when used concurrently with appropriate antituberculous chemotherapy; trichinosis with neurologic or myocardial involvement.

In addition to the above indications, prednisone tablets are indicated for systemic dermatomyositis (polymyositis).

CONTRAINDICATIONS

Prednisone tablets are contraindicated in systemic fungal infections and known hypersensitivity to components.

WARNINGS

In patients on corticosteroid therapy subjected to unusual stress, increased dosage of rapidly acting corticosteroids before, during and after the stressful situation is indicated.

Immunosuppression and Increased Risk of Infection

Corticosteroids, including prednisone tablets, suppress the immune system and increase the risk of infection with any pathogen, including viral, bacterial, fungal, protozoan, or helminthic pathogens. Corticosteroids can:

• Reduce resistance to new infections

• Exacerbate existing infections

• Increase the risk of disseminated infections

• Increase the risk of reactivation or exacerbation of latent infections

• Mask some signs of infection

Corticosteroid-associated infections can be mild but can be severe and at times fatal. The rate of infectious complications increases with increasing corticosteroid dosages.

Monitor for the development of infection and consider prednisone tablets withdrawal or dosage reduction as needed.

Tuberculosis

If prednisone tablets is used to treat a condition in patients with latent tuberculosis or tuberculin reactivity, reactivation of tuberculosis may occur. Closely monitor such patients for reactivation. During prolonged prednisone tablets therapy, patients with latent tuberculosis or tuberculin reactivity should receive chemoprophylaxis.

Varicella Zoster and Measles Viral Infections

Varicella and measles can have a serious or even fatal course in non-immune patients taking corticosteroids, including prednisone tablets. In corticosteroid-treated patients who have not had these diseases or are non-immune, particular care should be taken to avoid exposure to varicella and measles:

• If a prednisone tablets-treated patient is exposed to varicella, prophylaxis with varicella zoster immune globulin may be indicated. If varicella develops, treatment with antiviral agents may be considered.

• If a prednisone tablets-treated patient is exposed to measles, prophylaxis with immunoglobulin may be indicated.

Hepatitis B Virus Reactivation

Hepatitis B virus reactivation can occur in patients who are hepatitis B carriers treated with immunosuppressive dosages of corticosteroids, including prednisone tablets. Reactivation can also occur infrequently in corticosteroid-treated patients who appear to have resolved hepatitis B infection. Screen patients for hepatitis B infection before initiating immunosuppressive (e.g., prolonged) treatment with prednisone tablets. For patients who show evidence of hepatitis B infection, recommend consultation with physicians with expertise in managing hepatitis B regarding monitoring and consideration for hepatitis B antiviral therapy.

Fungal Infections

Corticosteroids, including prednisone tablets, may exacerbate systemic fungal infections; therefore, avoid prednisone tablets use in the presence of such infections unless prednisone tablets is needed to control drug reactions. For patients on chronic prednisone tablets therapy who develop systemic fungal infections, prednisone tablets withdrawal or dosage reduction is recommended.

Amebiasis

Corticosteroids, including prednisone tablets, may activate latent amebiasis. Therefore, it is recommended that latent amebiasis or active amebiasis be ruled out before initiating prednisone tablets in patients who have spent time in the tropics or patients with unexplained diarrhea.

Strongyloides Infestation

Corticosteroids, including prednisone tablets, should be used with great care in patients with known or suspected Strongyloides (threadworm) infestation. In such patients, corticosteroid-induced immunosuppression may lead to Strongyloides hyperinfection and dissemination with widespread larval migration, often accompanied by severe enterocolitis and potentially fatal gram-negative septicemia.

Cerebral Malaria

Avoid corticosteroids, including prednisone tablets, in patients with cerebral malaria.

Kaposi's Sarcoma

Kaposi's sarcoma has been reported to occur in patients receiving corticosteroid therapy, most often for chronic conditions. Discontinuation of corticosteroids may result in clinical improvement of Kaposi's sarcoma.

Prolonged use of corticosteroids may produce posterior subcapsular cataracts, glaucoma with possible damage to the optic nerves, and may enhance the establishment of secondary ocular infections due to fungi or viruses.

Usage in pregnancy: Since adequate human reproduction studies have not been done with corticosteroids, the use of these drugs in pregnancy, nursing mothers or women of childbearing potential requires that the possible benefits of the drug be weighed against the potential hazards to the mother and embryo or fetus. Infants born of mothers who have received substantial doses of corticosteroids during pregnancy should be carefully observed for signs of hypoadrenalism.

Average and large doses of hydrocortisone or cortisone can cause elevation of blood pressure, salt and water retention, and increased excretion of potassium. These effects are less likely to occur with the synthetic derivatives except when used in large doses. Dietary salt restriction and potassium supplementation may be necessary. All corticosteroids increase calcium excretion.

While on corticosteroid therapy patients should not be vaccinated against smallpox. Other immunization procedures should not be undertaken in patients who are on corticosteroids, especially on high doses, because of possible hazards of neurological complications and a lack of antibody response.

PRECAUTIONS

Information for Patients

Persons who are on immunosuppressant doses of corticosteroids should be warned to avoid exposure to chickenpox or measles. Patients should also be advised that if they are exposed, medical advice should be sought without delay.

General: Drug-induced, secondary adrenocortical insufficiency may be minimized by gradual reduction of dosage. This type of relative insufficiency may persist for months after discontinuation of therapy; therefore, in any situation of stress occurring during that period, hormone therapy should be reinstituted. Since mineralocorticoid secretion may be impaired, salt and/or a mineralocorticoid should be administered concurrently.

There is an enhanced effect of corticosteroids in patients with hypothyroidism and in those with cirrhosis.

Corticosteroids should be used cautiously in patients with ocular herpes simplex because of possible corneal perforation.

The lowest possible dose of corticosteroid should be used to control the condition under treatment, and when reduction in dosage is possible, the reduction should be gradual.

Psychic derangements may appear when corticosteroids are used, ranging from euphoria, insomnia, mood swings, personality changes, and severe depression to frank psychotic manifestations. Also, existing emotional instability or psychotic tendencies may be aggravated by corticosteroids.

Aspirin should be used cautiously in conjunction with corticosteroids in hypoprothrombinemia.

Steroids should be used with caution in: nonspecific ulcerative colitis, if there is a probability of impending perforation, abscess or other pyogenic infection; diverticulitis; fresh intestinal anastomoses; active or latent peptic ulcer; renal insufficiency; hypertension; osteoporosis; and myasthenia gravis.

Growth and development of infants and children on prolonged corticosteroid therapy should be carefully observed.

ADVERSE REACTIONS

The following adverse reactions have been reported with prednisone or other corticosteroids:

Fluid and electrolyte disturbances: sodium retention, fluid retention, congestive heart failure in susceptible patients, potassium loss, hypokalemic alkalosis, hypertension.

Musculoskeletal: muscle weakness, steroid myopathy, loss of muscle mass, osteoporosis, vertebral compression fractures, aseptic necrosis of femoral and humeral heads, pathologic fracture of long bones.

Gastrointestinal: peptic ulcer with possible perforation and hemorrhage, pancreatitis, abdominal distention, ulcerative esophagitis.

Dermatologic: impaired wound healing, thin fragile skin, petechiae and ecchymoses, facial erythema, increased sweating, may suppress reactions to skin tests.

Neurological: convulsions, increased intracranial pressure with papilledema (pseudotumorcerebri) usually after treatment, vertigo, headache.

Endocrine: menstrual irregularities; development of cushingoid state; suppression of growth in children; secondary adrenocortical and pituitary unresponsiveness, particularly in times of stress, as in trauma, surgery or illness; decreased carbohydrate tolerance; manifestations of latent diabetes mellitus; increased requirements of insulin or oral hypoglycemic agents in diabetics.

Ophthalmic: posterior subcapsular cataracts, increased intraocular pressure, glaucoma, exophthalmos.

Metabolic: negative nitrogen balance due to protein catabolism.

To report SUSPECTED ADVERSE REACTIONS, contact Strides Pharma Inc. at 1-877-244-9825 or FDA at 1-800-FDA-1088 or www.fda.gov/medwatch

DOSAGE AND ADMINISTRATION

Dosage of prednisone tablets should be individualized according to the severity of the disease and the response of the patient. For infants and children, the recommended dosage should be governed by the same considerations rather than strict adherence to the ratio indicated by age or body weight.

Hormone therapy is an adjunct to, and not a replacement for, conventional therapy.

Dosage should be decreased or discontinued gradually when the drug has been administered for more than a few days.

The severity, prognosis, expected duration of the disease, and the reaction of the patient to medication are primary factors in determining dosage.

If a period of spontaneous remission occurs in a chronic condition, treatment should be discontinued.

Blood pressure, body weight, routine laboratory studies, including two-hour postprandial blood glucose and serum potassium, and a chest X-ray should be obtained at regular intervals during prolonged therapy. Upper GI X-rays are desirable in patients with known or suspected peptic ulcer disease.

The initial dosage of prednisone may vary from 5 mg to 60 mg per day, depending on the specific disease entity being treated. In situations of less severity lower doses will generally suffice, while in selected patients higher initial doses may be required. The initial dosage should be maintained or adjusted until a satisfactory response is noted. If after a reasonable period of time there is a lack of satisfactory clinical response, prednisone should be discontinued and the patient transferred to other appropriate therapy. IT SHOULD BE EMPHASIZED THAT DOSAGE REQUIREMENTS ARE VARIABLE AND MUST BE INDIVIDUALIZED ON THE BASIS OF THE DISEASE UNDER TREATMENT AND THE RESPONSE OF THE PATIENT. After a favourable response is noted, the proper maintenance dosage should be determined by decreasing the initial drug dosage in small decrements at appropriate time intervals until the lowest dosage which will maintain an adequate clinical response is reached. It should be kept in mind that constant monitoring is needed in regard to drug dosage. Included in the situations which may make dosage adjustments necessary are changes in clinical status secondary to remissions or exacerbations in the disease process, the patient's individual drug responsiveness, and the effect of patient exposure to stressful situations not directly related to the disease entity under treatment; in this latter situation it may be necessary to increase the dosage of prednisone for a period of time consistent with the patient's condition. If after long-term therapy the drug is to be stopped, it is recommended that it be withdrawn gradually rather than abruptly.

HOW SUPPLIED

PredniSONE Tablets USP

1 mg - white to off white color, circular, biconvex tablets debossed with "P1" on one side and break line on other side.

Product Name | NDC Number | Pack Type
Prednisone Tablets USP, 1 mg | 64380-782-06 | 100's Count in HDPE container
Prednisone Tablets USP, 1 mg | 64380-782-01 | 10 x 10's count blister pack

Store at 20° to 25 °C (68° to 77 °F); excursions permitted to 15° to 30 °C (59° to 86 °F) [see USP Controlled Room Temperature].

Dispense in a tight, child-resistant container as defined in the USP/NF.

PROTECT FROM MOISTURE.

Manufactured by:

Strides Pharma Science Limited

Bengaluru - 562106, India.

Distributed by:

Strides Pharma Inc.

Bridgewater, NJ 08807

Revised: 07/2025

PACKAGE LABEL.PRINCIPAL DISPLAY PANEL

NDC 64380-782-06

PredniSONE Tablets, USP

1 mg

100 Tablets

Rx only

Strides Pharma Inc.